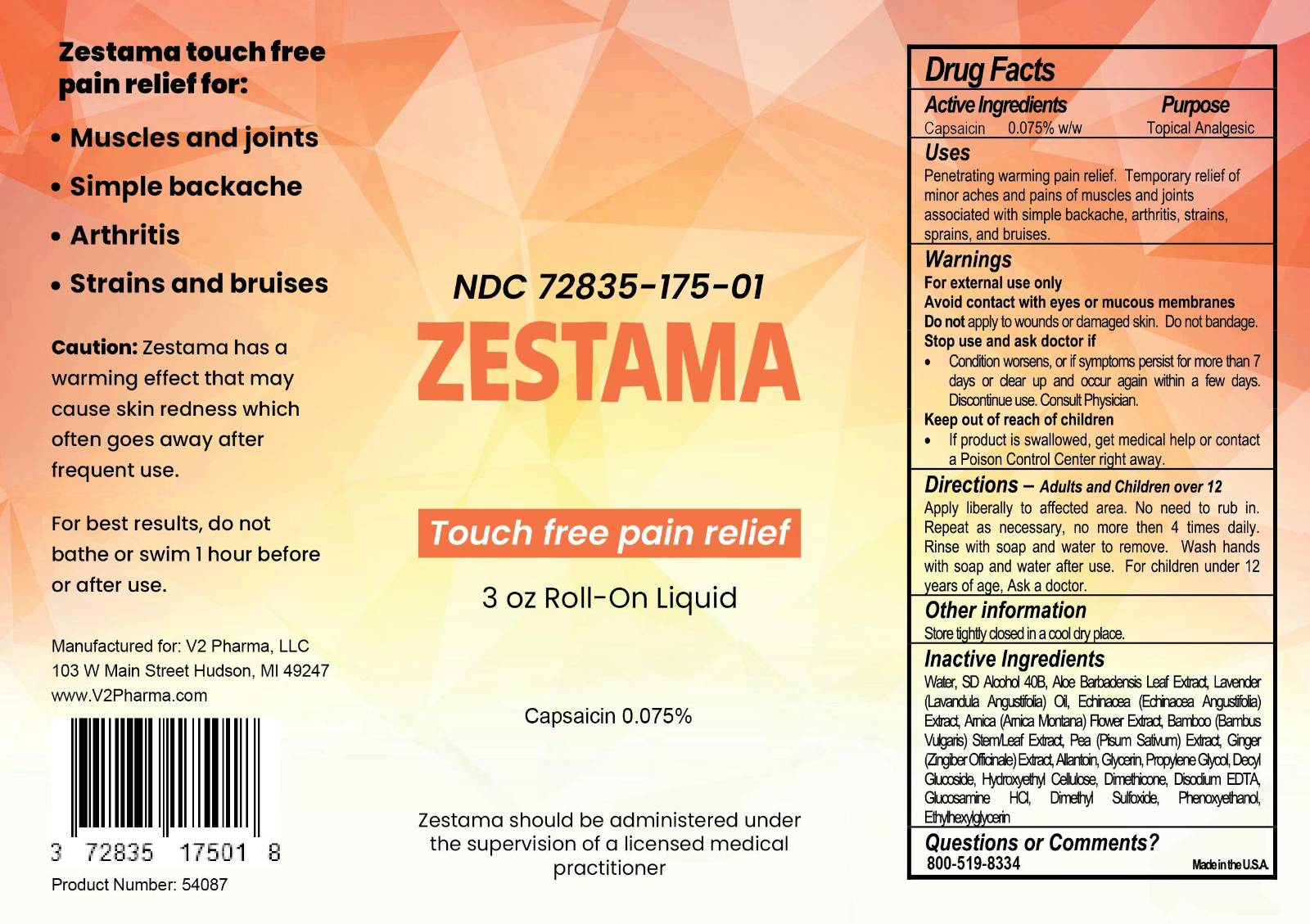 DRUG LABEL: Zestama
NDC: 72835-175 | Form: LIQUID
Manufacturer: V2 Pharma LLC
Category: otc | Type: HUMAN OTC DRUG LABEL
Date: 20251215

ACTIVE INGREDIENTS: CAPSAICIN 0.075 g/100 mL
INACTIVE INGREDIENTS: WATER; DIMETHICONE; ALCOHOL; DIMETHYL SULFOXIDE; LAVENDER OIL; DECYL GLUCOSIDE; GINGER; BAMBUSA VULGARIS TOP; PEA; GLUCOSAMINE HCL; ARNICA MONTANA FLOWER; PROPYLENE GLYCOL; PHENOXYETHANOL; ETHYLHEXYLGLYCERIN; HYDROXYETHYL CELLULOSE (5500 MPA.S AT 2%); ALLANTOIN; ECHINACEA PURPUREA ROOT; ALOE BARBADENSIS LEAF; EDETATE DISODIUM

Zestama

Zestama

Touch free pain relief

Uses

Temporarily relieves minor aches and pains of muscles and joints associated with:

- simple backache
- arthritis
- strains
- sprains
- bruises

Directions Adults and children 12 years of age and older:

Apply Zestama using the touch free roll-on applicator to affected area liberally as needed for pain. Do not use more than 4 times per day.

For children under 12 years of age, ask a doctor.

Fore external use only

Read all warnings and directions before use.

Test first on small area of skin.

When using this product you may experience a burning sensation and/or skin redness. The intensity of this reaction varies among individuals and may be severe. With regular use, this generally disappears after several days.

Do not use:

- Near the face, eyes, or genetalia
- Immediately before or after bathing or swimming
- On wounds or damaged skin
- If you are allergic to capsicum or chili peppers
- Do not bandage

Stop use and ask a doctor or pharmacist if:

- Condition worsens or does not improve after regular use
- Severe burning persists or blistering occurs
- Treated area skin begins to scale or peel as if burnt

Instructions for Zestama Touch Free Pain Relief:

- Lightly shake and invert bottle to allow product into applicator.
- Remove cap to expose applicator. Try not to touch any surfaces or liquids.
- Avoid contact with the eyes, lips, nose, genetalia and other mucous membranes.
- Invert the bottle, then apply liberally to affected area 3 to 4 times daily.
- Do not use hands to rub in.
- Place cap back on and Wash hands thoroughly with soap and water.
- Allow treated area to dry naturally for best results.
- Do not swim or bathe for at least 1 hour.
- Do not tightly wrap or bandage the treated area
- Do not apply heat to the treated area immediately before or after use.
- Moisture and sweat can further “activate” the treated area and warm up more

STORAGE AND HANDLING

Store tightly closed in a cool dry place.

INACTIVE INGREDIENT

Water
Dimethicone
Alcohol
Dimethyl Sulfoxide
Lavender Oil
Decyl Glucoside
Ginger Extract
Bamboo Extract
Pea Extract
Glucosamine HCI
Arnica Extract
Propylene Glycol
Phenoxyethanol
Ethylhexylglycerin
Hydroxyethyl Cellulose
Allantoin
Echinacea Extract
Aloe Barbadensis Leaf Extract
Disodium EDTA

Manufactured for:

V2 Pharma, LLC

103 W Main Street

Hudson, MI 49247